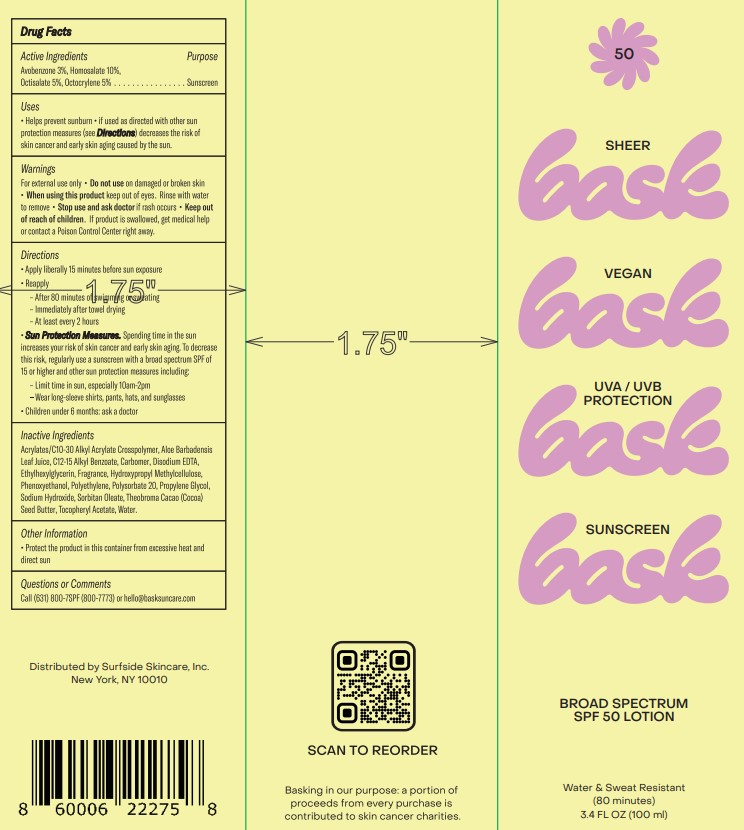 DRUG LABEL: Hurley
NDC: 58443-0586 | Form: LOTION
Manufacturer: Prime Enterprises Inc.
Category: otc | Type: HUMAN OTC DRUG LABEL
Date: 20221111

ACTIVE INGREDIENTS: AVOBENZONE 29.19 g/1 mL; OCTISALATE 48.65 g/1 mL; OCTOCRYLENE 48.65 g/1 mL; HOMOSALATE 97.3 g/1 mL
INACTIVE INGREDIENTS: HYPROMELLOSE, UNSPECIFIED; SORBITAN MONOOLEATE; POLYSORBATE 20; COCOA BUTTER; WATER; SODIUM HYDROXIDE; PHENOXYETHANOL; ETHYLHEXYLGLYCERIN; PROPYLENE GLYCOL; ALOE VERA LEAF; .ALPHA.-TOCOPHEROL ACETATE; EDETATE DISODIUM; HIGH DENSITY POLYETHYLENE; CARBOMER INTERPOLYMER TYPE A (ALLYL SUCROSE CROSSLINKED); ALKYL (C12-15) BENZOATE; CARBOMER 980

BASK Broad Spectrum SPF 50 Lotion

Active Ingredients

Avobenzone 3%

Homosalate 10%

Octisalate 5%

Octocrylene 5%

Purpose

Sunscreen

Uses

• Helps prevent sunburn

• If used as directed with other sun protection measures (See Directions), decreases the risk of skin cancer and early skin aging caused by the sun.

Warnings

For external use only

Do not use

on damaged or broken skin

When using this product

keep out of eyes. Rinse with water to remove.

Stop use and ask a doctor if

rash occurs.

Keep out of reach of children.

If product is swallowed, get medical help or contact a Poison Control Center right away.

Directions

• Apply liberally 15 minutes before sun exposure.

• Reapply:

• After 80 minutes of swimming or sweating

• Immediately after towel drying

• At least every 2 hours

• Sun Protection Measures. Spending time in the sun increases your risk of skin cancer and early skin aging. To decrease this risk, regularly use a sunscreen with a broad spectrum SPF of 15 or higher and other sun protection measures including:

• Limit time in the sun, especially from 10 a.m. – 2 p.m.

• Wear long-sleeve shirts, pants, hats, and sunglasses.

• Children under 6 months: Ask a doctor.

Inactive Ingredients

Acrylates/C10-30 Alkyl Acrylate Crosspolymer, Aloe Barbadensis Leaf Juice, C12-15 Alkyl Benzoate, Carbomer, Disodium EDTA, Ethylhexylglycerin, Fragrance, Hydroxypropyl Methylcellulose, Phenoxyethanol, Polyethylene, Polysorbate 20, Propylene Glycol, Sodium Hydroxide, Sorbitan Oleate, Theobroma Cacao (Cocoa) Seed Butter, Tocopheryl Acetate, Water

Other Information

• Protect the product in this container from excessive heat and direct sun

Questions or Comments?

Call(631) 800-7SPF(800-7773) or hello@basksuncare.com